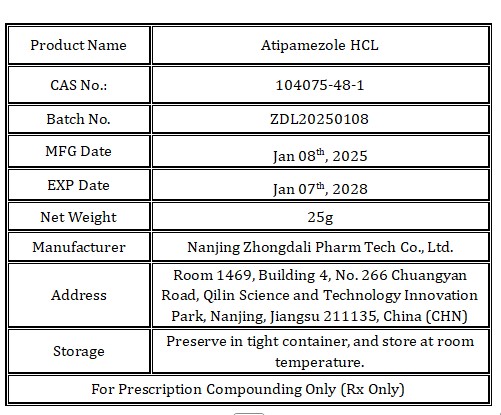 DRUG LABEL: Atipamezole HCL
NDC: 86225-019 | Form: POWDER
Manufacturer: Nanjing Zhongdali Pharm Tech Co., Ltd.
Category: other | Type: BULK INGREDIENT - ANIMAL DRUG
Date: 20250626

ACTIVE INGREDIENTS: Atipamezole hydrochloride 1 kg/1 kg

Atipamezole HCL